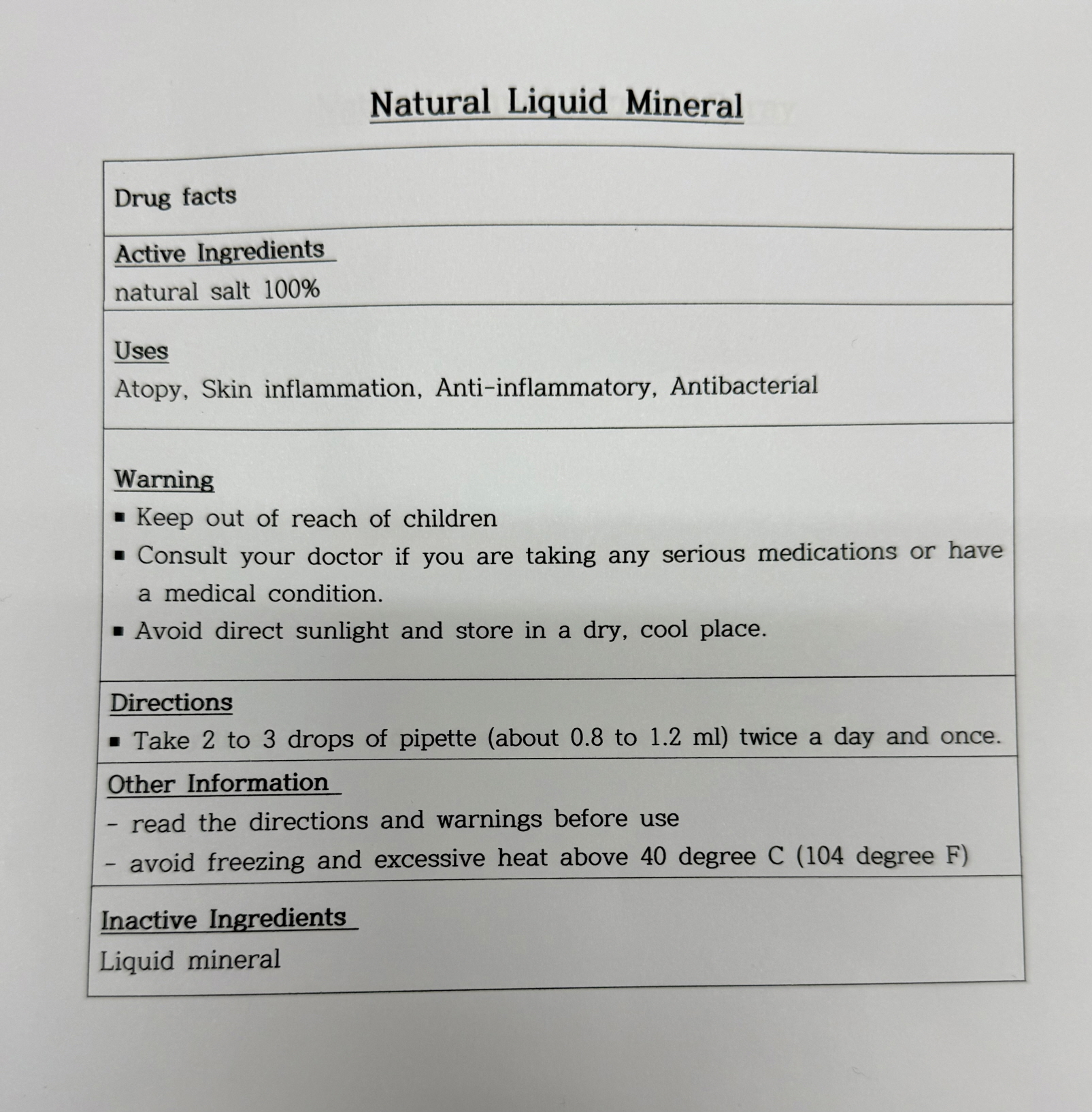 DRUG LABEL: NATURAL LIQUIDMINERAL
NDC: 87034-0003 | Form: LIQUID
Manufacturer: K-LA-KO Co.,LTD
Category: otc | Type: HUMAN OTC DRUG LABEL
Date: 20250821

ACTIVE INGREDIENTS: SODIUM CHLORIDE 100 g/100 mL
INACTIVE INGREDIENTS: WATER

Drug Facts

ACTIVE INGREDIENT

NATURAL SALT 100%

INACTIVE INGREDIENT

Liquid mineral

PURPOSE

Atopy, Skin inflammation, Anti-inflammatory, Antibacterial

keep out of reach of the children

INDICATIONS AND USAGE

Take 2 to 3 drops of pipette (about 0.8 to 1.2 ml) twice a day and once.

WARNINGS

Consult your doctor if you are taking any serious medication or have a medical condition

Avoid direct sunlight and store in a dry, cool place.

Read the directions and warnings before use.

Avoid freezing and excessive heat abouve 40 degree C (104 degree F)

DOSAGE AND ADMINISTRATION

topical use only